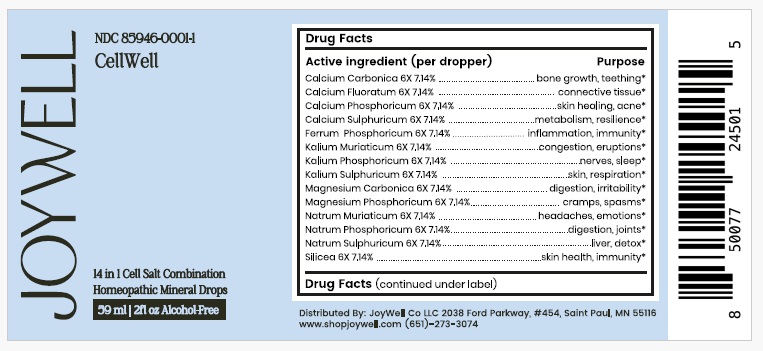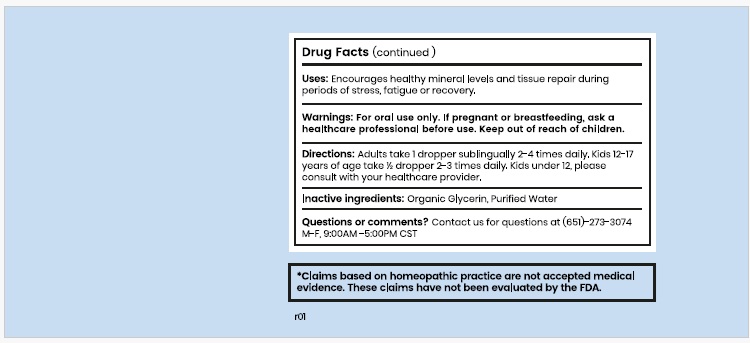 DRUG LABEL: Cell Well
NDC: 85946-0001 | Form: LIQUID
Manufacturer: JoyWell Co LLC
Category: homeopathic | Type: HUMAN OTC DRUG LABEL
Date: 20251211

ACTIVE INGREDIENTS: OYSTER SHELL CALCIUM CARBONATE, CRUDE 6 [hp_X]/60 mL; CALCIUM FLUORIDE 6 [hp_X]/60 mL; CALCIUM PHOSPHATE, UNSPECIFIED FORM 6 [hp_X]/60 mL; CALCIUM SULFATE, UNSPECIFIED FORM 6 [hp_X]/60 mL; FERROSOFERRIC PHOSPHATE 6 [hp_X]/60 mL; POTASSIUM CHLORIDE 6 [hp_X]/60 mL; POTASSIUM PHOSPHATE, UNSPECIFIED FORM 6 [hp_X]/60 mL; POTASSIUM SULFATE 6 [hp_X]/60 mL; MAGNESIUM CARBONATE 6 [hp_X]/60 mL; MAGNESIUM PHOSPHATE ANHYDROUS 6 [hp_X]/60 mL; SODIUM CHLORIDE 6 [hp_X]/60 mL; SODIUM PHOSPHATE, DIBASIC, HEPTAHYDRATE 6 [hp_Q]/60 mL; SODIUM SULFATE 6 [hp_X]/60 mL; SILICON DIOXIDE 6 [hp_Q]/60 mL
INACTIVE INGREDIENTS: WATER; GLYCERIN

Active ingredients Purpose

Calcium Carbonica 6X 7.14% bone growth, teething*
Calcium Fluoratum 6X 7.14% connective tissue*
Calcium Phosphoricum 6X 7.14% skin healing, acne*
Calcium Sulphuricum 6X 7.14% metabolism, resilience*
Ferrum Phosphoricum 6X 7.14% inflammation, immunity*
Kalium Muriaticum 6X 7.14% congestion, eruptions*
Kalium Phosphoricum 6X 7.14% nerves, sleep*
Kalium Sulphuricum 6X 7.14% skin, respiration*
Magnesium Carbonica 6X 7.14% digestion, irritability*
Magnesium Phosphoricum 6X 7.14% cramps, spasms*
Natrum Muriaticum 6X 7.14% headaches, emotions*
Natrum Phosphoricum 6X 7.14% digestion, joints*
Natrum Sulphuricum 6X 7.14% liver, detox*
Silicea 6X 7.14% skin health, immunity*

* Claims based on homeopathic practice are not accepted medical evidence. These claims have not been evaluated by the FDA.

Uses

Encourages healthy mineral levels and tissue repair during periods of stress, fatigue or recovery.

Warnings

For oral use only. If pregnant or breast-feeding, ask a health care professional before use. Keep out of the reach of children.

Directions

Adults take 1 dropper sublingually 2-4 times daily. Kids 12-17 years of age take ½ dropper 2-3 times daily.

Kids under 12, please consult with your healthcare provider.

Inactive ingredients

Organic Glycerin, Purified water

QUESTIONS OR COMMENTS?

Contact us for questions at (651)-273-3074-M-F, 9.00AM -5.00PM CST